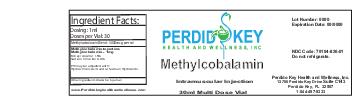 DRUG LABEL: Methylcobalamin
NDC: 70104-826 | Form: INJECTION
Manufacturer: Perdido Key Health and Wellness Inc
Category: prescription | Type: HUMAN PRESCRIPTION DRUG LABEL
Date: 20151120

ACTIVE INGREDIENTS: METHYLCOBALAMIN 1 mg/1 mL

DOSAGE FORMS AND STRENGTHS

1mL